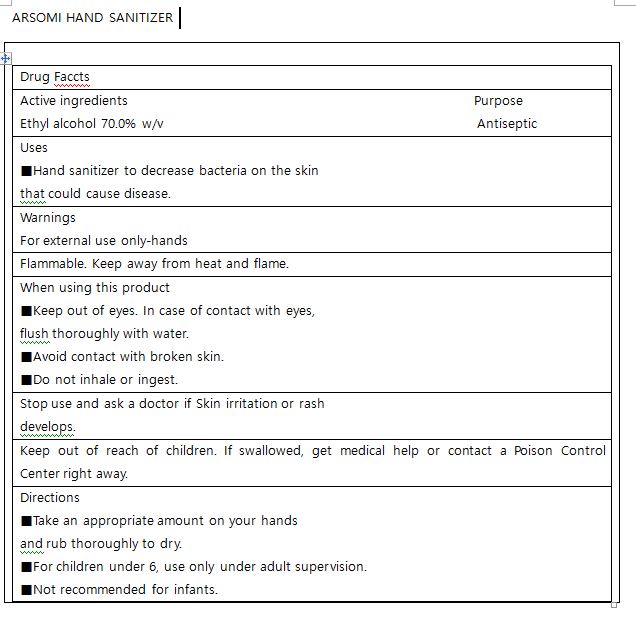 DRUG LABEL: ARSOMI HAND SANITIZER
NDC: 76677-0002 | Form: GEL
Manufacturer: ESON
Category: otc | Type: HUMAN OTC DRUG LABEL
Date: 20200430

ACTIVE INGREDIENTS: ALCOHOL 70 mL/100 mL
INACTIVE INGREDIENTS: ALOE ARBORESCENS LEAF; GLYCERIN; POLYSORBATE 80; .ALPHA.-TOCOPHEROL ACETATE; CARBOMER 940; TROLAMINE; WATER

Drug Facts

ACTIVE INGREDIENT

alcohol

INACTIVE INGREDIENT

ethanol, water, glycerin, polysorbate 80, carbomer, aloe arborescens leaf extract, triethanolamine, tocopheryl acetate

PURPOSE

Sterilization of hands and skin

KEEP OUT OF REACH OF THE CHILDREN

INDICATIONS AND USAGE

Apply to clean, dry hands. Apply sufficient amount to thoroughly wet all surfaces of hands and fingers. Rub onto hands until dry.

Supervise children in the use of this product.

WARNINGS

■ Flammable. Keep away from fire or flame.

■ For external use only.

■ Do not use in eyes.

■ lf swallowed, get medical help promptly.

■ Stop use, ask doctor lf irritation occurs.

■ Keep out of reach of children.

DOSAGE AND ADMINISTRATION

for external use only